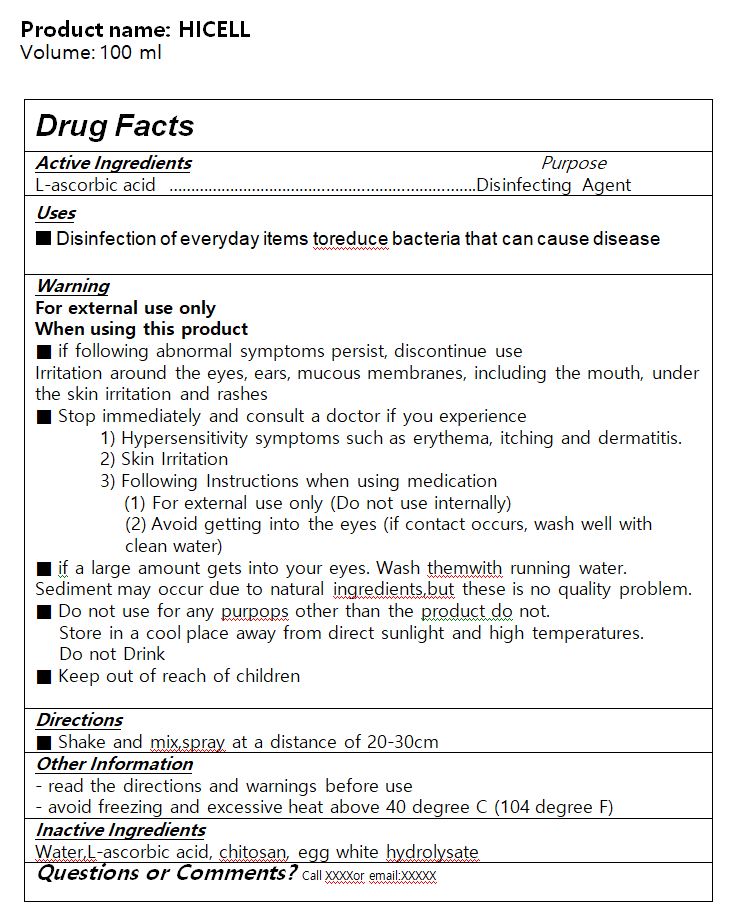 DRUG LABEL: New Clairfore
NDC: 75768-0005 | Form: LIQUID
Manufacturer: ORGANELLE Inc
Category: otc | Type: HUMAN OTC DRUG LABEL
Date: 20211224

ACTIVE INGREDIENTS: ASCORBIC ACID 5 g/100 mL
INACTIVE INGREDIENTS: WATER

Drug Facts

ACTIVE INGREDIENT

L-ascorbic acid

INACTIVE INGREDIENT

Water, chitosan, egg white hydrolysate

KEEP OUT OF REACH OF THE CHILDREN

PURPOSE

hand sanitizer to help reduce bacteria that potentially can cause disease

for use when soap and water are not available

INDICATIONS AND USAGE

Place enough product on hands to cover all surfaces.Rub hands together until dry.
Supervise children under 6 years of age when using this product to avoid swallowing.

WARNINGS

For external use only.

Flammable, keep away from fire or flame.

When using this product keep out of eyes. If contact with eyes occurs, rinse promptly and thoroughly with water.

Stop use and ask a doctor if significant irritation or sensitization develops.

Keep out of reach of children. If swallowed, get medical help or contact a Poison Control Center right away.

DOSAGE AND ADMINISTRATION

for external use only